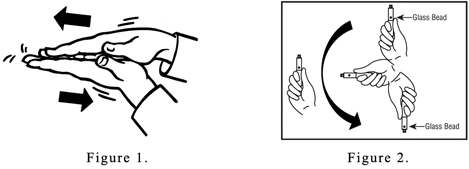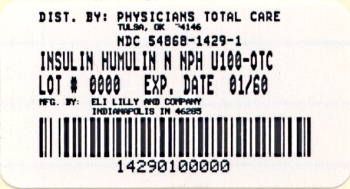 DRUG LABEL: Humulin N
NDC: 54868-1429 | Form: INJECTION, SUSPENSION
Manufacturer: Physicians Total Care, Inc.
Category: otc | Type: HUMAN OTC DRUG LABEL
Date: 20101108

ACTIVE INGREDIENTS: INSULIN HUMAN 100 [iU]/1 mL
INACTIVE INGREDIENTS: GLYCERIN 16 mg/1 mL; METACRESOL 1.6 mg/1 mL; ZINC 0.025 mg/1 mL; PHENOL 0.65 mg/1 mL; PROTAMINE SULFATE 0.35 mg/1 mL; SODIUM PHOSPHATE, DIBASIC 3.78 mg/1 mL; WATER; HYDROCHLORIC ACID; SODIUM HYDROXIDE

INFORMATION FOR THE PATIENT
10 mL Vial (1000 Units per vial)
3 mL Vial (300 Units per vial)

WARNINGS

THIS LILLY HUMAN INSULIN PRODUCT DIFFERS FROM ANIMAL–SOURCE INSULINS BECAUSE IT IS STRUCTURALLY IDENTICAL TO THE INSULIN PRODUCED BY YOUR BODY’S PANCREAS AND BECAUSE OF ITS UNIQUE MANUFACTURING PROCESS.

ANY CHANGE OF INSULIN SHOULD BE MADE CAUTIOUSLY AND ONLY UNDER MEDICAL SUPERVISION. CHANGES IN STRENGTH, MANUFACTURER, TYPE (E.G., REGULAR, NPH, ANALOG), SPECIES, OR METHOD OF MANUFACTURE MAY RESULT IN THE NEED FOR A CHANGE IN DOSAGE.

SOME PATIENTS TAKING HUMULIN® (HUMAN INSULIN, rDNA ORIGIN) MAY REQUIRE A CHANGE IN DOSAGE FROM THAT USED WITH OTHER INSULINS. IF AN ADJUSTMENT IS NEEDED, IT MAY OCCUR WITH THE FIRST DOSE OR DURING THE FIRST SEVERAL WEEKS OR MONTHS.

DIABETES

Insulin is a hormone produced by the pancreas, a large gland that lies near the stomach. This hormone is necessary for the body’s correct use of food, especially sugar. Diabetes occurs when the pancreas does not make enough insulin to meet your body’s needs.

To control your diabetes, your doctor has prescribed injections of insulin products to keep your blood glucose at a near–normal level. You have been instructed to test your blood and/or your urine regularly for glucose. Studies have shown that some chronic complications of diabetes such as eye disease, kidney disease, and nerve disease can be significantly reduced if the blood sugar is maintained as close to normal as possible. The American Diabetes Association recommends that if your pre–meal glucose levels are consistently above 130 mg/dL or your hemoglobin A1c (HbA1c) is more than 7%, you should talk to your doctor. A change in your diabetes therapy may be needed. If your blood tests consistently show below–normal glucose levels, you should also let your doctor know. Proper control of your diabetes requires close and constant cooperation with your doctor. Despite diabetes, you can lead an active and healthy life if you eat a balanced diet, exercise regularly, and take your insulin injections as prescribed by your doctor.

Always keep an extra supply of insulin as well as a spare syringe and needle on hand. Always wear diabetic identification so that appropriate treatment can be given if complications occur away from home.

DESCRIPTION

NPH HUMAN INSULIN

Description

Humulin is synthesized in a special non–disease–producing laboratory strain of Escherichia coli bacteria that has been genetically altered to produce human insulin. Humulin N [Human insulin (rDNA origin) isophane suspension] is a crystalline suspension of human insulin with protamine and zinc providing an intermediate-acting insulin with a slower onset of action and a longer duration of activity (up to 24 hours) than that of Regular human insulin. The time course of action of any insulin may vary considerably in different individuals or at different times in the same individual. As with all insulin preparations, the duration of action of Humulin N is dependent on dose, site of injection, blood supply, temperature, and physical activity. Humulin N is a sterile suspension and is for subcutaneous injection only. It should not be used intravenously or intramuscularly. The concentration of Humulin N is 100 units/mL (U–100).

Identification

Human insulin from Eli Lilly and Company has the trademark Humulin. Your doctor has prescribed the type of insulin that he/she believes is best for you.

DO NOT USE ANY OTHER INSULIN EXCEPT ON YOUR DOCTOR’S ADVICE AND DIRECTION.

Always check the carton and the bottle label for the name and letter designation of the insulin you receive from your pharmacy to make sure it is the same as prescribed by your doctor.

Always check the appearance of your bottle of Humulin N before withdrawing each dose. Before each injection the Humulin N bottle must be carefully shaken or rotated several times to completely mix the insulin. Humulin N suspension should look uniformly cloudy or milky after mixing. If not, repeat the above steps until contents are mixed. Do not use Humulin N:

- if the insulin substance (the white material) remains at the bottom of the bottle after mixing or
- if there are clumps in the insulin after mixing, or
- if solid white particles stick to the bottom or wall of the bottle, giving a frosted appearance.

If you see anything unusual in the appearance of Humulin N suspension in your bottle or notice your insulin requirements changing, talk to your doctor.

ACTIVE INGREDIENT

Insulin human | 100 [iU] in 1 mL

INACTIVE INGREDIENT

Glycerin | 16 mg in 1 mL
METACRESOL | 1.6 mg in 1 mL
Zinc | 0.025 mg in 1 mL
Phenol | 0.65 mg in 1 mL
PROTAMINE SULFATE | 0.35 mg in 1 mL
Sodium phosphate, dibasic | 3.78 mg in 1 mL
Water
Hydrochloric acid
Sodium hydroxide

Storage

Not in-use (unopened): Humulin N bottles not in-use should be stored in a refrigerator, but not in the freezer.

In-use (opened): The Humulin N bottle you are currently using can be kept unrefrigerated as long as it is kept as cool as possible [below 86°F (30°C)] away from heat and light.

Do not use Humulin N after the expiration date stamped on the label or if it has been frozen.

INDICATIONS AND USAGE

INSTRUCTIONS FOR INSULIN VIAL USE

NEVER SHARE NEEDLES AND SYRINGES.

Correct Syringe Type

Doses of insulin are measured in units. U–100 insulin contains 100 units/mL (1 mL=1 cc). With Humulin N, it is important to use a syringe that is marked for U–100 insulin preparations. Failure to use the proper syringe can lead to a mistake in dosage, causing serious problems for you, such as a blood glucose level that is too low or too high.

Syringe Use

To help avoid contamination and possible infection, follow these instructions exactly.

Disposable syringes and needles should be used only once and then discarded by placing the used needle in a puncture-resistant disposable container. Properly dispose of the puncture-resistant container as directed by your Health Care Professional.

Preparing the Dose

1. Wash your hands.
2. Carefully shake or rotate the bottle of insulin several times to completely mix the insulin.
3. Inspect the insulin. Humulin N suspension should look uniformly cloudy or milky. Do not use Humulin N if you notice anything unusual in its appearance.
4. If using a new Humulin N bottle, flip off the plastic protective cap, but do not remove the stopper. Wipe the top of the bottle with an alcohol swab.
5. If you are mixing insulins, refer to the “Mixing Humulin N and Regular Human Insulin” section below.
6. Draw an amount of air into the syringe that is equal to the Humulin N dose. Put the needle through rubber top of the Humulin N bottle and inject the air into the bottle.
7. Turn the Humulin N bottle and syringe upside down. Hold the bottle and syringe firmly in one hand and shake gently.
8. Making sure the tip of the needle is in the Humulin N suspension, withdraw the correct dose of Humulin N into the syringe.
9. Before removing the needle from the Humulin N bottle, check the syringe for air bubbles. If bubbles are present, hold the syringe straight up and tap its side until the bubbles float to the top. Push the bubbles out with the plunger and then withdraw the correct dose.
10. Remove the needle from the bottle and lay the syringe down so that the needle does not touch anything.
11. If you do not need to mix your Humulin N with Regular human insulin, go to the “Injection Instructions” section below and follow the directions.

Mixing Humulin N and Regular Human Insulin (Humulin R)

1. Humulin N should be mixed with Humulin R only on the advice of your doctor.
2. Draw an amount of air into the syringe that is equal to the amount of Humulin N you are taking. Insert the needle into the Humulin N bottle and inject the air. Withdraw the needle.
3. Draw an amount of air into the syringe that is equal to the amount of Humulin R you are taking. Insert the needle into the Humulin R bottle and inject the air, but do not withdraw the needle.
4. Turn the Humulin R bottle and syringe upside down.
5. Making sure the tip of the needle is in the Humulin R solution, withdraw the correct dose of Humulin R into the syringe.
6. Before removing the needle from the Humulin R bottle, check the syringe for air bubbles. If bubbles are present, hold the syringe straight up and tap its side until the bubbles float to the top. Push the bubbles out with the plunger and then withdraw the correct dose.
7. Remove the syringe with the needle from the Humulin R bottle and insert it into the Humulin N bottle. Turn the Humulin N bottle and syringe upside down. Hold the bottle and syringe firmly in one hand and shake gently. Making sure the tip of the needle is in the Humulin N, withdraw the correct dose of Humulin N.
8. Remove the needle from the bottle and lay the syringe down so that the needle does not touch anything.
9. Follow the directions under “Injection Instructions” section below.

Follow your doctor’s instructions on whether to mix your insulins ahead of time or just before giving your injection. It is important to be consistent in your method.

Syringes from different manufacturers may vary in the amount of space between the bottom line and the needle. Because of this, do not change:

- the sequence of mixing, or
- the model and brand of syringe or needle that your doctor has prescribed.

Injection Instructions

1. To avoid tissue damage, choose a site for each injection that is at least 1/2 inch from the previous injection site. The usual sites of injection are abdomen, thighs, and arms.
2. Cleanse the skin with alcohol where the injection is to be made.
3. With one hand, stabilize the skin by spreading it or pinching up a large area.
4. Insert the needle as instructed by your doctor.
5. Push the plunger in as far as it will go.
6. Pull the needle out and apply gentle pressure over the injection site for several seconds. Do not rub the area.
7. Place the used needle in a puncture-resistant disposable container and properly dispose of the puncture-resistant container as directed by your Health Care Professional.

DOSAGE

Your doctor has told you which insulin to use, how much, and when and how often to inject it. Because each patient’s diabetes is different, this schedule has been individualized for you.

Your usual dose of Humulin N may be affected by changes in your diet, activity, or work schedule. Carefully follow your doctor’s instructions to allow for these changes. Other things that may affect your Humulin N dose are:

Illness

Illness, especially with nausea and vomiting, may cause your insulin requirements to change. Even if you are not eating, you will still require insulin. You and your doctor should establish a sick day plan for you to use in case of illness. When you are sick, test your blood glucose frequently. If instructed by your doctor, test your ketones and report the results to your doctor.

Pregnancy

Good control of diabetes is especially important for you and your unborn baby. Pregnancy may make managing your diabetes more difficult. If you are planning to have a baby, are pregnant, or are nursing a baby, talk to your doctor.

Medication

Insulin requirements may be increased if you are taking other drugs with blood–glucose–raising activity, such as oral contraceptives, corticosteroids, or thyroid replacement therapy. Insulin requirements may be reduced in the presence of drugs that lower blood glucose or affect how your body responds to insulin, such as oral antidiabetic agents, salicylates (for example, aspirin), sulfa antibiotics, alcohol, certain antidepressants and some kidney and blood pressure medicines. Your Health Care Professional may be aware of other medications that may affect your diabetes control. Therefore, always discuss any medications you are taking with your doctor.

Exercise

Exercise may lower your body’s need for insulin during and for some time after the physical activity. Exercise may also speed up the effect of an insulin dose, especially if the exercise involves the area of injection site (for example, the leg should not be used for injection just prior to running). Discuss with your doctor how you should adjust your insulin regimen to accommodate exercise.

Travel

When traveling across more than 2 time zones, you should talk to your doctor concerning adjustments in your insulin schedule.

COMMON PROBLEMS OF DIABETES

Hypoglycemia (Low Blood Sugar)

Hypoglycemia (too little glucose in the blood) is one of the most frequent adverse events experienced by insulin users. It can be brought about by:

1. Missing or delaying meals.
2. Taking too much insulin.
3. Exercising or working more than usual.
4. An infection or illness associated with diarrhea or vomiting.
5. A change in the body’s need for insulin.
6. Diseases of the adrenal, pituitary, or thyroid gland, or progression of kidney or liver disease.
7. Interactions with certain drugs, such as oral antidiabetic agents, salicylates (for example, aspirin), sulfa antibiotics, certain antidepressants and some kidney and blood pressure medicines.
8. Consumption of alcoholic beverages.

Symptoms of mild to moderate hypoglycemia may occur suddenly and can include:

- sweating

- drowsiness

- dizziness

- sleep disturbances

- palpitation

- anxiety

- tremor

- blurred vision

- hunger

- slurred speech

- restlessness

- depressed mood

- tingling in the hands, feet, lips, or tongue

- irritability

- lightheadedness

- abnormal behavior

- inability to concentrate

- unsteady movement

- headache

- personality changes

Signs of severe hypoglycemia can include:

- disorientation

- seizures

- unconsciousness

- death

Therefore, it is important that assistance be obtained immediately.

Early warning symptoms of hypoglycemia may be different or less pronounced under certain conditions, such as long duration of diabetes, diabetic nerve disease, use of medications such as beta–blockers, changing insulin preparations, or intensified control (3 or more insulin injections per day) of diabetes.

A few patients who have experienced hypoglycemic reactions after transfer from animal–source insulin to human insulin have reported that the early warning symptoms of hypoglycemia were less pronounced or different from those experienced with their previous insulin.

Without recognition of early warning symptoms, you may not be able to take steps to avoid more serious hypoglycemia. Be alert for all of the various types of symptoms that may indicate hypoglycemia. Patients who experience hypoglycemia without early warning symptoms should monitor their blood glucose frequently, especially prior to activities such as driving. If the blood glucose is below your normal fasting glucose, you should consider eating or drinking sugar–containing foods to treat your hypoglycemia.

Mild to moderate hypoglycemia may be treated by eating foods or drinks that contain sugar. Patients should always carry a quick source of sugar, such as hard candy or glucose tablets. More severe hypoglycemia may require the assistance of another person. Patients who are unable to take sugar orally or who are unconscious require an injection of glucagon or should be treated with intravenous administration of glucose at a medical facility.

You should learn to recognize your own symptoms of hypoglycemia. If you are uncertain about these symptoms, you should monitor your blood glucose frequently to help you learn to recognize the symptoms that you experience with hypoglycemia.

If you have frequent episodes of hypoglycemia or experience difficulty in recognizing the symptoms, you should talk to your doctor to discuss possible changes in therapy, meal plans, and/or exercise programs to help you avoid hypoglycemia.

Hyperglycemia (High Blood Sugar) and Diabetic Ketoacidosis (DKA)

Hyperglycemia (too much glucose in the blood) may develop if your body has too little insulin. Hyperglycemia can be brought about by any of the following:

1. Omitting your insulin or taking less than your doctor has prescribed.
2. Eating significantly more than your meal plan suggests.
3. Developing a fever, infection, or other significant stressful situation.

In patients with type 1 or insulin–dependent diabetes, prolonged hyperglycemia can result in DKA (a life-threatening emergency). The first symptoms of DKA usually come on gradually, over a period of hours or days, and include a drowsy feeling, flushed face, thirst, loss of appetite, and fruity odor on the breath. With DKA, blood and urine tests show large amounts of glucose and ketones. Heavy breathing and a rapid pulse are more severe symptoms. If uncorrected, prolonged hyperglycemia or DKA can lead to nausea, vomiting, stomach pain, dehydration, loss of consciousness, or death. Therefore, it is important that you obtain medical assistance immediately.

Lipodystrophy

Rarely, administration of insulin subcutaneously can result in lipoatrophy (seen as an apparent depression of the skin) or lipohypertrophy (seen as a raised area of the skin). If you notice either of these conditions, talk to your doctor. A change in your injection technique may help alleviate the problem.

Allergy

Local Allergy — Patients occasionally experience redness, swelling, and itching at the site of injection. This condition, called local allergy, usually clears up in a few days to a few weeks. In some instances, this condition may be related to factors other than insulin, such as irritants in the skin cleansing agent or poor injection technique. If you have local reactions, talk to your doctor.

Systemic Allergy — Less common, but potentially more serious, is generalized allergy to insulin, which may cause rash over the whole body, shortness of breath, wheezing, reduction in blood pressure, fast pulse, or sweating. Severe cases of generalized allergy may be life threatening. If you think you are having a generalized allergic reaction to insulin, call your doctor immediately.

ADDITIONAL INFORMATION

Information about diabetes may be obtained from your diabetes educator.

Additional information about diabetes and Humulin can be obtained by calling The Lilly Answers Center at 1-800-LillyRx (1-800-545-5979) or by visiting www.LillyDiabetes.com.

Patient Information revised September 2, 2009

10 mL Vials manufactured by
Eli Lilly and Company, Indianapolis, IN 46285, USA or
Lilly France, F-67640 Fegersheim, France
3 mL Vials manufactured by
Eli Lilly and Company, Indianapolis, IN 46285, USA

for Eli Lilly and Company, Indianapolis, IN 46285, USA

Copyright © 1997, 2009, Eli Lilly and Company. All rights reserved.

PV 5713 AMP

Relabeling of "Additional Barcode Label" by:
Physicians Total Care, Inc.
Tulsa, OK 74146

INFORMATION FOR THE PATIENT
3 ML PREFILLED INSULIN DELIVERY DEVICE
HUMULIN® N Pen
NPH
HUMAN INSULIN
(rDNA ORIGIN) ISOPHANE SUSPENSION
100 UNITS PER ML (U-100)

WARNINGS

THIS LILLY HUMAN INSULIN PRODUCT DIFFERS FROM ANIMAL–SOURCE INSULINS BECAUSE IT IS STRUCTURALLY IDENTICAL TO THE INSULIN PRODUCED BY YOUR BODY’S PANCREAS AND BECAUSE OF ITS UNIQUE MANUFACTURING PROCESS.

ANY CHANGE OF INSULIN SHOULD BE MADE CAUTIOUSLY AND ONLY UNDER MEDICAL SUPERVISION. CHANGES IN STRENGTH, MANUFACTURER, TYPE (E.G., REGULAR, NPH, ANALOG), SPECIES, OR METHOD OF MANUFACTURE MAY RESULT IN THE NEED FOR A CHANGE IN DOSAGE.

SOME PATIENTS TAKING HUMULIN® (HUMAN INSULIN, rDNA ORIGIN) MAY REQUIRE A CHANGE IN DOSAGE FROM THAT USED WITH OTHER INSULINS. IF AN ADJUSTMENT IS NEEDED, IT MAY OCCUR WITH THE FIRST DOSE OR DURING THE FIRST SEVERAL WEEKS OR MONTHS.

TO OBTAIN AN ACCURATE DOSE, CAREFULLY READ AND FOLLOW THE INSULIN DELIVERY DEVICE USER MANUAL AND THIS “INFORMATION FOR THE PATIENT” INSERT BEFORE USING THIS PRODUCT.

THE PEN MUST BE PRIMED TO A STREAM OF INSULIN (NOT JUST A FEW DROPS) BEFORE EACH INJECTION TO MAKE SURE THE PEN IS READY TO DOSE. YOU MAY NEED TO PRIME A NEW PEN UP TO SIX TIMES BEFORE A STREAM OF INSULIN APPEARS.

PRIMING THE PEN IS IMPORTANT TO CONFIRM THAT INSULIN COMES OUT WHEN YOU PUSH THE INJECTION BUTTON AND TO REMOVE AIR THAT MAY COLLECT IN THE INSULIN CARTRIDGE DURING NORMAL USE. IF YOU DO NOT PRIME, YOU MAY RECEIVE TOO MUCH OR TOO LITTLE INSULIN (see also INSTRUCTIONS FOR INSULIN PEN USE section).

DIABETES

Insulin is a hormone produced by the pancreas, a large gland that lies near the stomach. This hormone is necessary for the body’s correct use of food, especially sugar. Diabetes occurs when the pancreas does not make enough insulin to meet your body’s needs.

To control your diabetes, your doctor has prescribed injections of insulin products to keep your blood glucose at a near–normal level. You have been instructed to test your blood and/or your urine regularly for glucose. Studies have shown that some chronic complications of diabetes such as eye disease, kidney disease, and nerve disease can be significantly reduced if the blood sugar is maintained as close to normal as possible. The American Diabetes Association recommends that if your pre-meal glucose levels are consistently above 130 mg/dL or your hemoglobin A1c (HbA1c) is more than 7%, you should talk to your doctor. A change in your diabetes therapy may be needed. If your blood tests consistently show below–normal glucose levels, you should also let your doctor know. Proper control of your diabetes requires close and constant cooperation with your doctor. Despite diabetes, you can lead an active and healthy life if you eat a balanced diet, exercise regularly, and take your insulin injections as prescribed by your doctor.

Always keep an extra supply of insulin as well as a spare syringe and needle on hand. Always wear diabetic identification so that appropriate treatment can be given if complications occur away from home.

NPH HUMAN INSULIN

Description

Humulin is synthesized in a special non–disease–producing laboratory strain of Escherichia coli bacteria that has been genetically altered to produce human insulin. Humulin N [Human insulin (rDNA origin) isophane suspension] is a crystalline suspension of human insulin with protamine and zinc providing an intermediate-acting insulin with a slower onset of action and a longer duration of activity (up to 24 hours) than that of Regular human insulin. The time course of action of any insulin may vary considerably in different individuals or at different times in the same individual. As with all insulin preparations, the duration of action of Humulin N is dependent on dose, site of injection, blood supply, temperature, and physical activity. Humulin N is a sterile suspension and is for subcutaneous injection only. It should not be used intravenously or intramuscularly. The concentration of Humulin N is 100 units/mL (U–100).

Identification

Human insulin from Eli Lilly and Company has the trademark Humulin. Your doctor has prescribed the type of insulin that he/she believes is best for you.

DO NOT USE ANY OTHER INSULIN EXCEPT ON YOUR DOCTOR’S ADVICE AND DIRECTION.

The Humulin N Pen is available in boxes of 5 prefilled insulin delivery devices (“insulin Pens”). The Humulin N Pen is not designed to allow any other insulin to be mixed in its cartridge, or for the cartridge to be removed.

Always check the carton and the Pen label for the name and letter designation of the insulin you receive from your pharmacy to make sure it is the same as prescribed by your doctor.

Always check the appearance of Humulin N suspension in your insulin Pen before using. A cartridge of Humulin N contains a small glass bead to assist in mixing. Roll the Pen back and forth between the palms 10 times (see Figure 1). Gently turn the Pen up and down 10 times until the insulin is evenly mixed (see Figure 2).

If not evenly mixed, repeat the above steps until contents are mixed. Pens containing Humulin N suspension should be examined frequently.

Do not use Humulin N:

- if the insulin substance (the white material) remains visibly separated from the liquid after mixing or
- if there are clumps in the insulin after mixing, or
- if solid white particles stick to the walls of the cartridge, giving a frosted appearance.

If you see anything unusual in the appearance of the Humulin N suspension in your Pen or notice your insulin requirements changing, talk to your doctor.

Never attempt to remove the cartridge from the Humulin N Pen. Inspect the cartridge through the clear cartridge holder.

Storage

Not in-use (unopened): Humulin N Pens not in-use should be stored in a refrigerator, but not in the freezer.

In-use (opened): Humulin N Pens in-use should NOT be refrigerated but should be kept at room temperature [below 86°F (30°C)] away from direct heat and light. The Humulin N Pen you are currently using must be discarded 2 weeks after the first use, even if it still contains Humulin N.

Do not use Humulin N after the expiration date stamped on the label or if it has been frozen.

INSTRUCTIONS FOR INSULIN PEN USE

It is important to read, understand, and follow the instructions in the Insulin Delivery Device User Manual before using. Failure to follow instructions may result in getting too much or too little insulin. The needle must be changed and the Pen must be primed to a stream of insulin (not just a few drops) before each injection to make sure the Pen is ready to dose. You may need to prime a new Pen up to six times before a stream of insulin appears. Performing these steps before each injection is important to confirm that insulin comes out when you push the injection button, and to remove air that may collect in the insulin cartridge during normal use.

Every time you inject:

- Use a new needle.
- Prime to a stream of insulin (not just a few drops) to make sure the Pen is ready to dose.
- Make sure you got your full dose.

NEVER SHARE INSULIN PENS, CARTRIDGES, OR NEEDLES.

PREPARING FOR INJECTION

1. Wash your hands.
2. To avoid tissue damage, choose a site for each injection that is at least 1/2 inch from the previous injection site. The usual sites of injection are abdomen, thighs, and arms.
3. Follow the instructions in your Insulin Delivery Device User Manual to prepare for injection.
4. After injecting the dose, pull the needle out and apply gentle pressure over the injection site for several seconds. Do not rub the area.
5. After the injection, remove the needle from the Humulin N Pen. Do not reuse needles.
6. Place the used needle in a puncture-resistant disposable container and properly dispose of the puncture-resistant container as directed by your Health Care Professional.

DOSAGE

Your doctor has told you which insulin to use, how much, and when and how often to inject it. Because each patient’s diabetes is different, this schedule has been individualized for you.

Your usual dose of Humulin N may be affected by changes in your diet, activity, or work schedule. Carefully follow your doctor’s instructions to allow for these changes. Other things that may affect your Humulin N dose are:

Illness

Illness, especially with nausea and vomiting, may cause your insulin requirements to change. Even if you are not eating, you will still require insulin. You and your doctor should establish a sick day plan for you to use in case of illness. When you are sick, test your blood glucose frequently. If instructed by your doctor, test your ketones and report the results to your doctor.

Pregnancy

Good control of diabetes is especially important for you and your unborn baby. Pregnancy may make managing your diabetes more difficult. If you are planning to have a baby, are pregnant, or are nursing a baby, talk to your doctor.

Medication

Insulin requirements may be increased if you are taking other drugs with blood–glucose–raising activity, such as oral contraceptives, corticosteroids, or thyroid replacement therapy. Insulin requirements may be reduced in the presence of drugs that lower blood glucose or affect how your body responds to insulin, such as oral antidiabetic agents, salicylates (for example, aspirin), sulfa antibiotics, alcohol, certain antidepressants and some kidney and blood pressure medicines. Your Health Care Professional may be aware of other medications that may affect your diabetes control. Therefore, always discuss any medications you are taking with your doctor.

Exercise

Exercise may lower your body’s need for insulin during and for some time after the physical activity. Exercise may also speed up the effect of an insulin dose, especially if the exercise involves the area of injection site (for example, the leg should not be used for injection just prior to running). Discuss with your doctor how you should adjust your insulin regimen to accommodate exercise.

Travel

When traveling across more than 2 time zones, you should talk to your doctor concerning adjustments in your insulin schedule.

COMMON PROBLEMS OF DIABETES

Hypoglycemia (Low Blood Sugar)

Hypoglycemia (too little glucose in the blood) is one of the most frequent adverse events experienced by insulin users. It can be brought about by:

1. Missing or delaying meals.
2. Taking too much insulin.
3. Exercising or working more than usual.
4. An infection or illness associated with diarrhea or vomiting.
5. A change in the body’s need for insulin.
6. Diseases of the adrenal, pituitary, or thyroid gland, or progression of kidney or liver disease.
7. Interactions with certain drugs, such as oral antidiabetic agents, salicylates (for example, aspirin), sulfa antibiotics, certain antidepressants and some kidney and blood pressure medicines.
8. Consumption of alcoholic beverages.

Symptoms of mild to moderate hypoglycemia may occur suddenly and can include:

- sweating

- drowsiness

- dizziness

- sleep disturbances

- palpitation

- anxiety

- tremor

- blurred vision

- hunger

- slurred speech

- restlessness

- depressed mood

- tingling in the hands, feet, lips, or tongue

- irritability

- lightheadedness

- abnormal behavior

- inability to concentrate

- unsteady movement

- headache

- personality changes

Signs of severe hypoglycemia can include:

- disorientation

- seizures

- unconsciousness

- death

Therefore, it is important that assistance be obtained immediately.

Early warning symptoms of hypoglycemia may be different or less pronounced under certain conditions, such as long duration of diabetes, diabetic nerve disease, use of medications such as beta–blockers, changing insulin preparations, or intensified control (3 or more insulin injections per day) of diabetes.

A few patients who have experienced hypoglycemic reactions after transfer from animal–source insulin to human insulin have reported that the early warning symptoms of hypoglycemia were less pronounced or different from those experienced with their previous insulin.

Without recognition of early warning symptoms, you may not be able to take steps to avoid more serious hypoglycemia. Be alert for all of the various types of symptoms that may indicate hypoglycemia. Patients who experience hypoglycemia without early warning symptoms should monitor their blood glucose frequently, especially prior to activities such as driving. If the blood glucose is below your normal fasting glucose, you should consider eating or drinking sugar–containing foods to treat your hypoglycemia.

Mild to moderate hypoglycemia may be treated by eating foods or drinks that contain sugar. Patients should always carry a quick source of sugar, such as hard candy or glucose tablets. More severe hypoglycemia may require the assistance of another person. Patients who are unable to take sugar orally or who are unconscious require an injection of glucagon or should be treated with intravenous administration of glucose at a medical facility.

You should learn to recognize your own symptoms of hypoglycemia. If you are uncertain about these symptoms, you should monitor your blood glucose frequently to help you learn to recognize the symptoms that you experience with hypoglycemia.

If you have frequent episodes of hypoglycemia or experience difficulty in recognizing the symptoms, you should talk to your doctor to discuss possible changes in therapy, meal plans, and/or exercise programs to help you avoid hypoglycemia.

Hyperglycemia (High Blood Sugar) and Diabetic Ketoacidosis (DKA)

Hyperglycemia (too much glucose in the blood) may develop if your body has too little insulin. Hyperglycemia can be brought about by any of the following:

1. Omitting your insulin or taking less than your doctor has prescribed.
2. Eating significantly more than your meal plan suggests.
3. Developing a fever, infection, or other significant stressful situation.

In patients with type 1 or insulin–dependent diabetes, prolonged hyperglycemia can result in DKA (a life-threatening emergency). The first symptoms of DKA usually come on gradually, over a period of hours or days, and include a drowsy feeling, flushed face, thirst, loss of appetite, and fruity odor on the breath. With DKA, blood and urine tests show large amounts of glucose and ketones. Heavy breathing and a rapid pulse are more severe symptoms. If uncorrected, prolonged hyperglycemia or DKA can lead to nausea, vomiting, stomach pain, dehydration, loss of consciousness, or death. Therefore, it is important that you obtain medical assistance immediately.

Lipodystrophy

Rarely, administration of insulin subcutaneously can result in lipoatrophy (seen as an apparent depression of the skin) or lipohypertrophy (seen as a raised area of the skin). If you notice either of these conditions, talk to your doctor. A change in your injection technique may help alleviate the problem.

Allergy

Local Allergy — Patients occasionally experience redness, swelling, and itching at the site of injection. This condition, called local allergy, usually clears up in a few days to a few weeks. In some instances, this condition may be related to factors other than insulin, such as irritants in the skin cleansing agent or poor injection technique. If you have local reactions, talk to your doctor.

Systemic Allergy — Less common, but potentially more serious, is generalized allergy to insulin, which may cause rash over the whole body, shortness of breath, wheezing, reduction in blood pressure, fast pulse, or sweating. Severe cases of generalized allergy may be life threatening. If you think you are having a generalized allergic reaction to insulin, call your doctor immediately.

ADDITIONAL INFORMATION

Information about diabetes may be obtained from your diabetes educator.

Additional information about diabetes and Humulin can be obtained by calling The Lilly Answers Center at 1–800–LillyRx (1–800–545–5979) or by visiting www.LillyDiabetes.com.

Patient Information revised March 16, 2009

Pens manufactured by
Eli Lilly and Company, Indianapolis, IN 46285, USA or
Lilly France, F-67640 Fegersheim, France

for Eli Lilly and Company, Indianapolis, IN 46285, USA

Copyright © 1998, 2009, Eli Lilly and Company. All rights reserved.

PA 9135 FSAMP

PACKAGE LABELING

This section contains a representative sample of product package labeling. Product may be manufactured at multiple manufacturing sites. See the Additional Information section for a list of products and associated manufacturing sites.

PACKAGE CARTON – HUMULIN N Vial 10 mL 1ct

NDC 54868-1429-1

HI-310

10 mL

100 units per mL

Humulin® N

NPH

human insulin

(rDNA origin)

isophane suspension

For subcutaneous use only.

U-100